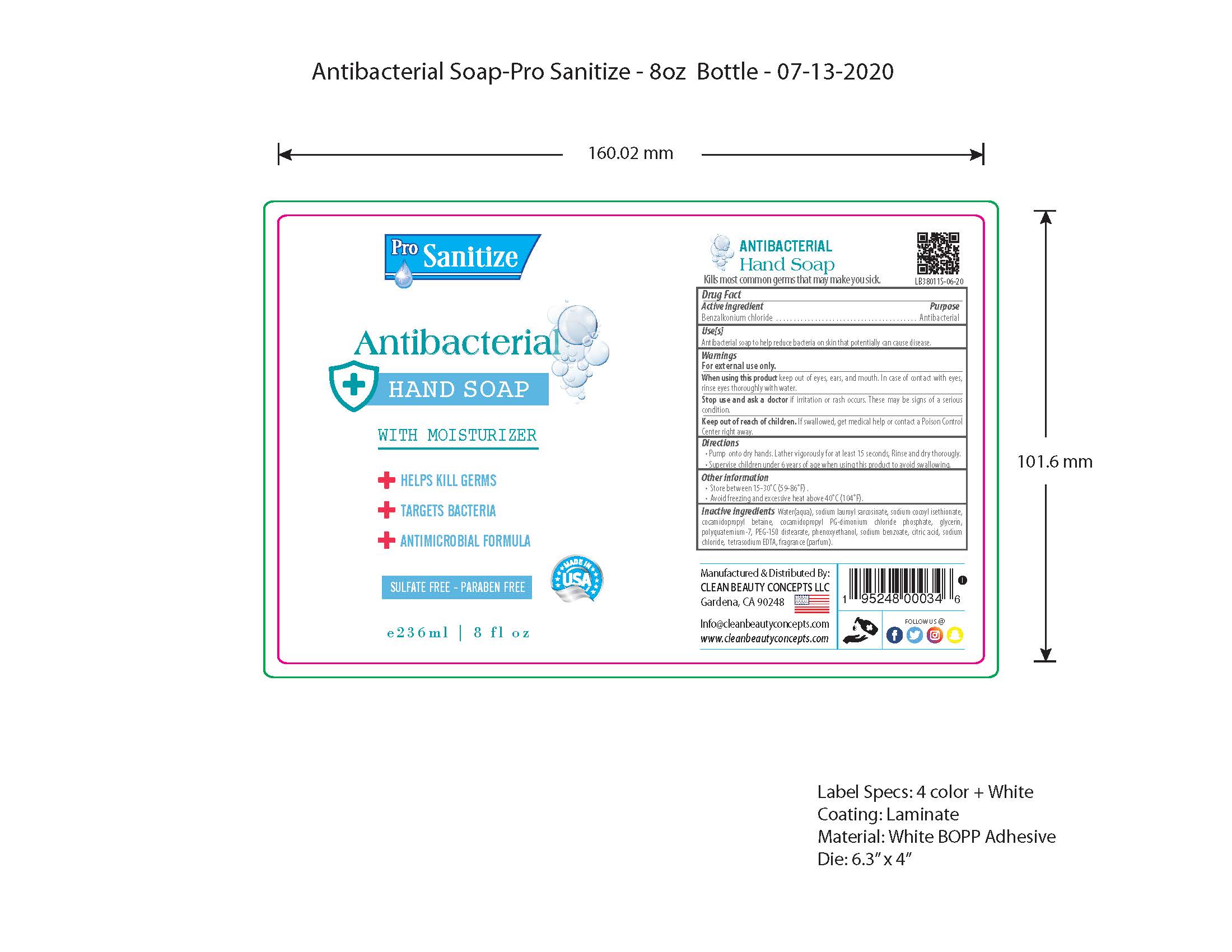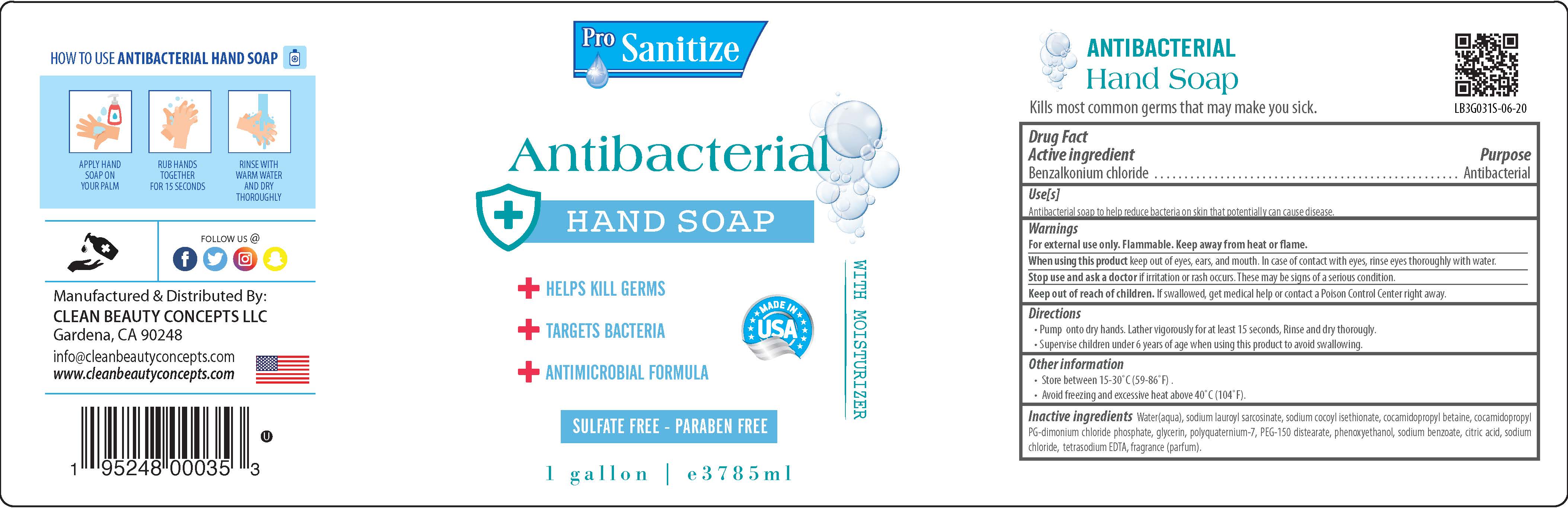 DRUG LABEL: Prosanitize
NDC: 76665-005 | Form: SOAP
Manufacturer: Clean Beauty Concepts
Category: otc | Type: HUMAN OTC DRUG LABEL
Date: 20200722

ACTIVE INGREDIENTS: BENZALKONIUM CHLORIDE 0.1 mg/100 mL
INACTIVE INGREDIENTS: POLYQUATERNIUM-7 (70/30 ACRYLAMIDE/DADMAC; 1600000 MW) 0.4 mL/100 mL; PHENOXYETHANOL 0.5 mL/100 mL; CITRIC ACID MONOHYDRATE 0.2 mL/100 mL; SODIUM CHLORIDE 0.5 mL/100 mL; FRAGRANCE LEMON ORC2001060 0.2 mL/100 mL; COCAMIDOPROPYL BETAINE 5 mL/100 mL; EDETATE SODIUM 0.05 mL/100 mL; SODIUM LAUROYL SARCOSINATE 9.25 mL/100 mL; GLYCERIN 0.3 mL/100 mL; SODIUM COCOYL ISETHIONATE 6.2 mL/100 mL; WATER 75.5 mL/100 mL; SODIUM BENZOATE 0.1 mL/100 mL; PEG-150 DISTEARATE 0.5 mL/100 mL; COCAMIDOPROPYL PG-DIMONIUM CHLORIDE PHOSPHATE 1.2 mL/100 mL

The hand soap is manufactured using only the following United States Pharmacopoeia (USP) grade ingredients:

1. Benzalkonium chloride
2. Water(aqua),
3. sodium lauroyl sarcosinate,
4. sodium cocoyl isethionate,
5. cocamidopropyl betaine,
6. cocamidopropyl
7. PG-dimonium chloride phosphate,
8. glycerin, polyquaternium-7,
9. PEG-150 distearate,
10. phenoxyethanol,
11. sodium benzoate,
12. citric acid,
13. sodium chloride,
14. tetrasodium EDTA,
15. fragrance (parfum).

Active Ingredient(s)

Benzalkonium chloride 0.1% v/v. Purpose: Antibacterial

Purpose

Antibacterial

Use

Antibacterial soap to help reduce bacteria on skin that potentially can cause disease.

Warnings

For external use only. Flammable. Keep away from heat or flame.

When using this product keep out of eyes, ears, and mouth. In case of contact with eyes, rinse eyes thoroughly with water.

Stop use and ask a doctor if irritation or rash occurs. These may be signs of a serious condition.

Keep out of reach of children. If swallowed, get medical help or contact a Poison Control Center right away.

Directions

• Pump onto dry hands. Lather vigorously for at least 15 seconds, Rinse and dry thorougly.
• Supervise children under 6 years of age when using this product to avoid swallowing.

Other information

- Store between 15-30°C (59-86°F) .
  • Avoid freezing and excessive heat above 40°C (104°F).

Inactive ingredients

Water(aqua), sodium lauroyl sarcosinate, sodium cocoyl isethionate, cocamidopropyl betaine, cocamidopropyl
PG-dimonium chloride phosphate, glycerin, polyquaternium-7, PEG-150 distearate, phenoxyethanol, sodium benzoate, citric acid, sodium chloride, tetrasodium EDTA, fragrance (parfum).

Package Label - Principal Display Panel

236 mL NDC: 76665-005-08

3785 mL NDC: 76665-005-01